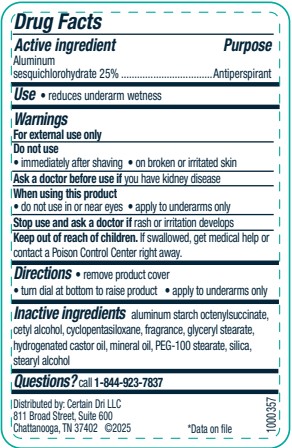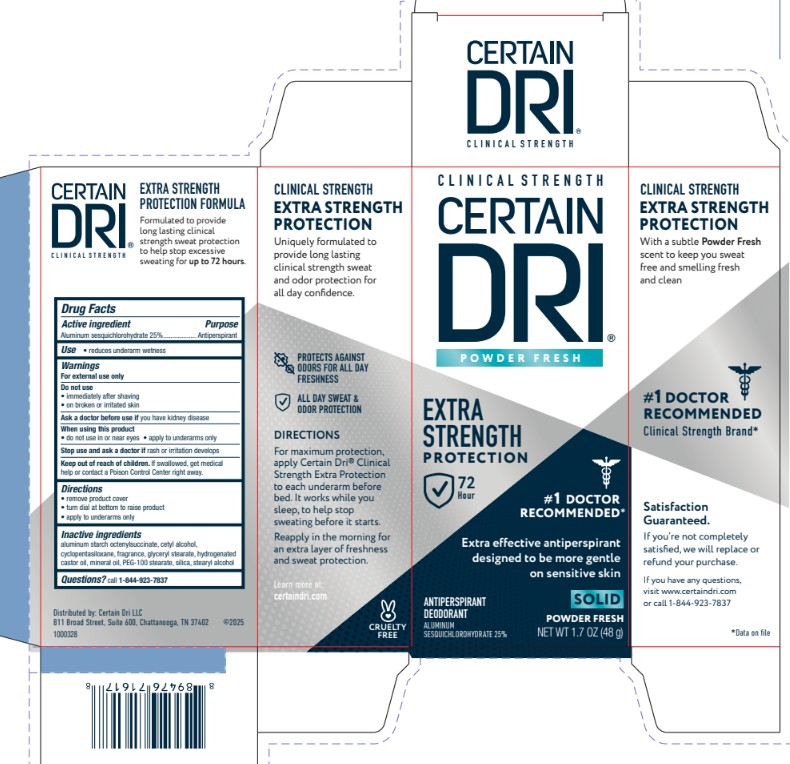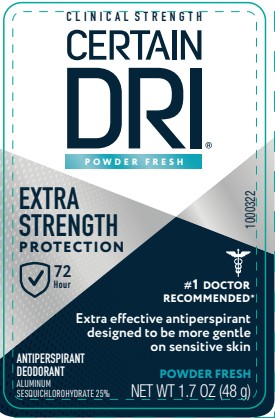 DRUG LABEL: Certain Dri Powder Fresh Extra Strength Protection
NDC: 69693-731 | Form: STICK
Manufacturer: Clarion Brands LLC
Category: otc | Type: HUMAN OTC DRUG LABEL
Date: 20251124

ACTIVE INGREDIENTS: ALUMINUM SESQUICHLOROHYDRATE 25 g/100 g
INACTIVE INGREDIENTS: GLYCERYL STEARATE; ALUMINUM STARCH OCTENYLSUCCINATE; CYCLOPENTASILOXANE; FRAGRANCE CLEAN ORC0600327; PEG-100 STEARATE; HYDROGENATED CASTOR OIL; STEARYL ALCOHOL; HYDRATED SILICA; CETYL ALCOHOL; MINERAL OIL

ACTIVE INGREDIENT

Aluminum sesquichlorohydrate 25%

PURPOSE

Antiperspirant

INDICATIONS AND USAGE

- reduces underarm wetness

WARNINGS

For external use only

Ask a doctor before use if you have kidney disease

DO NOT USE

- immediately afte shaving
- on broken or irritated skin

- do not use in or near eyes
- apply to underarms only

Stop use and ask a doctor if rash or irritation develops

Keep out of reach of children. If swallowed, get medical help or contact a Poison Control Center right away.

DOSAGE AND ADMINISTRATION

- remove product cover
- turn dial at bottom to raise product
- apply to underarms only

INACTIVE INGREDIENT

aluminum starch octenylsuccinate, cetyl alcohol, cyclopentasiloxane, fragrance, glyceryl stearate, hydrogenated castor oil, mineral oil, PEG-100 stearate, silica, stearyl alcohol

Questions? call 1-844-923-7837

PACKAGE LABEL

Clinical Strength

CERTAIN DRI®

POWDER FRESH

EXTRA STRENGTH PROTECTION

72 Hour

#1 Doctor Recommended

Extra effective antiperspirant designed to be more gentle on sensitive skin

SOLID POWDER FRESH

NET WT 1.7 OZ (48g)

ANTIPERSPIRANT DEODORANT

Aluminum Sesquichlorohydrate 25%

CLINICAL STRENGTH EXTRA STRENGTH PROTECTION

Uniquely formulated to provide long lasting clinical strength sweat and odor protection for all day confidence.

PROTECTS AGAINST ODORS FOR ALL DAY FRESHNESS

ALL DAY SWEAT & ODOR PROTECTION

DIRECTIONS
For maximum protection, apply Certain Dri® Clinical Strength Extra Protection to each underarm before bed. It works while you sleep, to help stop sweating before it starts.

Reapply in the morning for an extra layer of freshness and sweat protection.

Learn more at certaindri.com

CRUELTY FREE

CLINICAL STRENGTH EXTRA STRENGTH PROTECTION

With a subtle Powder Fresh scent to keep you sweat free and smelling fresh and clean

#1 DOCTOR RECOMMENDED*

Clinical Strength Brand

Satisfaction Guaranteed.

If you're not completely satisfied, we will replace or refund your purchase.

If you have any questions, visit www.certaindri.com or call 1-844-923-7837

*Data on file

CERTAIN DRI® CLINICAL STRENGTH

EXTRA STRENGTH PROTECTION FORMULA

Formulated to provide long lasting clinical strength sweat protection to help stop excessive sweating for up to 72 hours.

CLINICAL STRENGTH CERTAIN DRI® POWDER FRESH

EVERY STRENGTH PROTECTION 72 Hour

#1 Doctor Recommended

Extra effective antiperspirant designed to be more gentle on sensitive skin

ANTIPERSPIRANT DEODORANT Aluminum Sesquichlorohydrate 25%

POWDER FRESH NET WT 1.7 OZ (48 g)